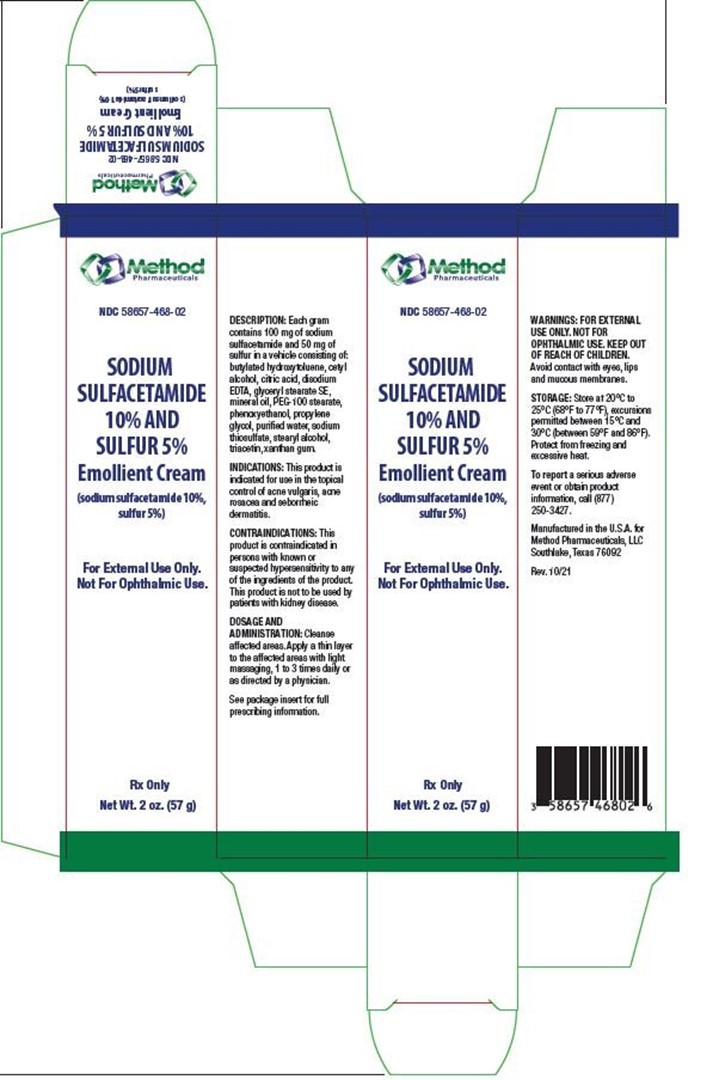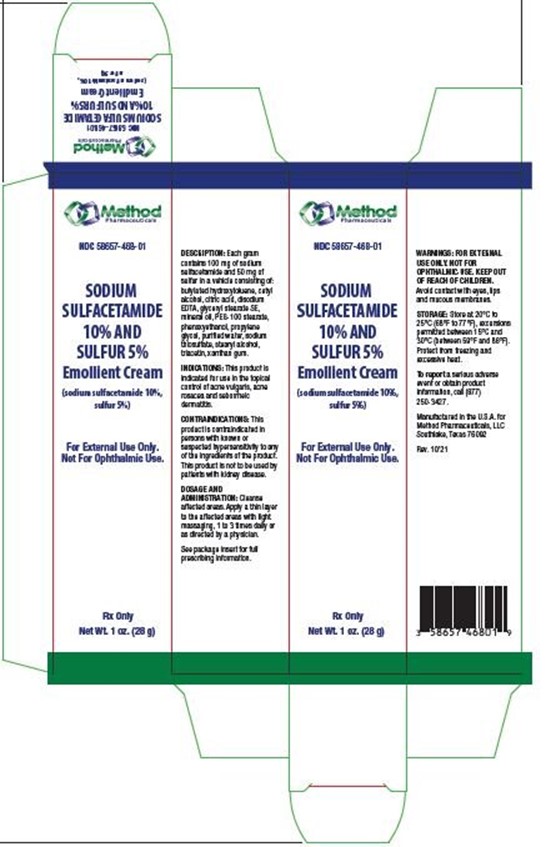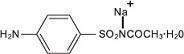 DRUG LABEL: SODIUM SULFACETAMIDE 10% AND SULFUR 5% Emollient Cream
NDC: 58657-468 | Form: CREAM
Manufacturer: Method Pharmaceuticals, LLC
Category: prescription | Type: HUMAN PRESCRIPTION DRUG LABEL
Date: 20260212

ACTIVE INGREDIENTS: SULFACETAMIDE SODIUM 100 mg/1 g; SULFUR 50 mg/1 g
INACTIVE INGREDIENTS: TRIACETIN; BUTYLATED HYDROXYTOLUENE; CETYL ALCOHOL; EDETATE DISODIUM; GLYCERYL STEARATE SE; PEG-100 STEARATE; MINERAL OIL; CITRIC ACID MONOHYDRATE; PHENOXYETHANOL; PROPYLENE GLYCOL; WATER; SODIUM THIOSULFATE; STEARYL ALCOHOL; XANTHAN GUM

Sodium Sulfacetamide 10% and Sulfur 5% Emollient Cream

DESCRIPTION:

Each gram contains 100 mg of sodium sulfacetamide and 50 mg of colloidal sulfur in a vehicle consisting of: butylated hydroxytoluene, cetyl alcohol, citric acid, disodium EDTA, glyceryl stearate SE, mineral oil, PEG-100 stearate, phenoxyethanol, propylene glycol, purified water, sodium thiosulfate, stearyl alcohol, triacetin, xanthan gum.

Sodium sulfacetamide is a sulfonamide with antibacterial activity while sulfur acts as a keratolytic agent. Sodium sulfacetamide is C8H9N2NaO3S·H2O with molecular weight of 254.24. Chemically, sodium sulfacetamid is N-[(4-aminophenyl) sulfonyl]-acetamide, monosodium salt, monohydrate. The structural formula is:

Sodium sulfacetamide is an odorless, white, crystalline powder with a bitter taste. It is freely soluble in water, sparingly soluble in alcohol, while practically insoluble in benzene, in chloroform and in ether.

CLINICAL PHARMACOLOGY:

Sodium sulfacetamide exerts a bacteriostatic effect against sulfonamide sensitive Gram-positive and Gram-negative microorganisms commonly isolated from secondary cutaneous pyogenic infections. It acts by restricting the synthesis of folic acid required by bacteria for growth, by its competition with para-aminobenzoic acid. There is no clinical data available on the degree and rate of systemic absorption of this product when applied to the skin or scalp. However, significant absorption of sodium sulfacetamide through the skin has been reported.

The following in vitro data is available, but the clinical significance is unknown. Organisms that show susceptibility to sodium sulfacetamide are: Streptococci, Staphylococci, E. coli, Klebsiella pneumoniae, Pseudomonas pyocyanea, Salmonella species, Proteus vulgaris, Nocardia and Actinomyces.

The exact mode of action of sulfur in the treatment of acne is unknown, but it has been reported that it inhibits the growth of Propionibacterium acnes and the formation of free fatty acids.

INDICATIONS:

This product is indicated for use in the topical control of acne vulgaris, acne rosacea and seborrheic dermatitis.

CONTRAINDICATIONS:

This product is contraindicated in persons with known or suspected hypersensitivity to any of the ingredients of the product. This product is not to be used by patients with kidney disease.

WARNINGS:

Sulfonamides are known to cause Stevens-Johnson syndrome in hypersensitive individuals. Stevens-Johnson syndrome also has been reported following the use of sodium sulfacetamide topically. Cases of drug-induced systemic lupus erythematosus from topical sulfacetamide also have been reported. In one of these cases, there was a fatal outcome.

KEEP OUT OF THE REACH OF CHILDREN.

FOR EXTERNAL USE ONLY. NOT FOR OPHTHALMIC USE.

General:

Nonsusceptible organisms, including fungi, may proliferate with the use of this preparation.

Although rare, sensitivity to sodium sulfacetamide may occur. Therefore, caution and careful supervision should be observed when prescribing this drug for patients who may be prone to hypersensitivity to topical sulfonamides. If the use of this product produces signs of hypersensitivity or other untoward reactions, discontinue use of the preparation. Patients should be carefully observed for possible local irritation or sensitization during long-term therapy. Systemic toxic reactions such as agranulocytosis, acute hemolytic anemia, purpura hemorrhagica, drug fever, jaundice and contact dermatitis indicate hypersensitivity to sulfonamides. Particular caution should be employed if areas of denuded or abraded skin are involved. Systemic absorption of topical sulfonamides is greater following application to large, infected, abraded, denuded, or severely burned areas. Under these circumstances, any of the adverse effects produced by the systemic administration of these agents could potentially occur, and appropriate observations and laboratory determinations should be performed.

The object of this therapy is to achieve desquamation without irritation, but sodium sulfacetamide and sulfur can cause reddening and scaling of the epidermis. These side effects are not unusual in the treatment of acne vulgaris, but patients should be cautioned about the possibility.

Information for Patients:

Patients should discontinue the use of this product if the condition becomes worse or if a rash develops in the area being treated or elsewhere. The use of this product also should be discontinued promptly, and the physician notified if any arthritis, fever, or sores in the mouth develop. Avoid contact with eyes, lips and mucous membranes.

Drug Interactions:

This product is incompatible with silver preparations.

Carcinogenesis, Mutagenesis, and Impairment of Fertility:

Long-term animal studies for carcinogenic potential have not been performed on this product to date. Studies on reproduction and fertility also have not been performed. Chromosomal nondisjunction has been reported in the yeast, Saccharomyces cerevisiae, following application of sodium sulfacetamide. The significance of this finding to the topical use of sodium sulfacetamide in the human is unknown.

Pregnancy:

Category C. Animal reproduction studies have not been conducted with this product. It is also not known whether this product can affect reproduction capacity or cause fetal harm when administered to a pregnant woman. This product should be used by a pregnant woman only if clearly needed or when potential benefits outweigh potential hazards to the fetus.

Nursing Mothers:

It is not known whether this drug is excreted in human milk. Because many drugs are excreted in human milk, caution should be exercised when this product is administered to a nursing woman.

Pediatric Use:

Safety and effectiveness in children under the age of 12 years have not been established.

ADVERSE REACTIONS:

Reports of irritation and hypersensitivity to sodium sulfacetamide are uncommon. The following adverse reactions, reported after administration of sterile ophthalmic sodium sulfacetamide, are noteworthy: instances of Stevens-Johnson syndrome and instances of local hypersensitivity which progressed to a syndrome resembling systemic lupus erythematosus; in one case a fatal outcome was reported (see WARNINGS).

OVERDOSAGE:

The oral LD 50 of sulfacetamide in mice is 16.5 g/kg. In the event of overdosage, emergency treatment should be started immediately.

Manifestations: Overdosage may cause nausea and vomiting. Large oral overdosage may cause hematuria, crystalluria and renal shutdown due to the precipitation of sulfa crystals in the renal tubules and the urinary tract. For treatment, contact your local Poison Control Center or your doctor.

DOSAGE AND ADMINISTRATION:

Cleanse affected areas. Apply a thin layer to the affected areas with light massaging, 1 to 3 times daily or as directed by a physician.

STORAGE:

Store at 20°C to 25°C (68°F to 77°F), excursions permitted between 15°C and 30°C (between 59°F and 86°F). Brief exposure to temperatures up to 40°C (104°F) may be tolerated provided the mean kinetic temperature does not exceed 25°C (77°F); however, such exposure should be minimized.

NOTICE:

Protect from freezing and excessive heat. The product may tend to darken slightly on storage. Slight discoloration does not impair the efficacy or safety of the product. Keep bottle tightly closed.

Occasionally, a slight discoloration of fabric may occur when an excessive amount of the product is used and comes in contact with white fabrics. This discoloration, however, presents no problem, as it is readily removed by ordinary laundering without bleaches.

HOW SUPPLIED:

This product is supplied in the following sizes:

1 oz. (28 g) bottles, NDC 58657-468-01

2 oz. (57 g) bottles, NDC 58657-468-02

To report a serious adverse event or obtain product information, call (877) 250-3427.

Manufactured in the U.S.A. for

Method Pharmaceuticals, LLC

Southlake, Texas 76092

PACKAGE LABEL

1 oz. (28 g) bottles, NDC 58657-468-01

2 oz. (57 g) bottles, NDC 58657-468-02